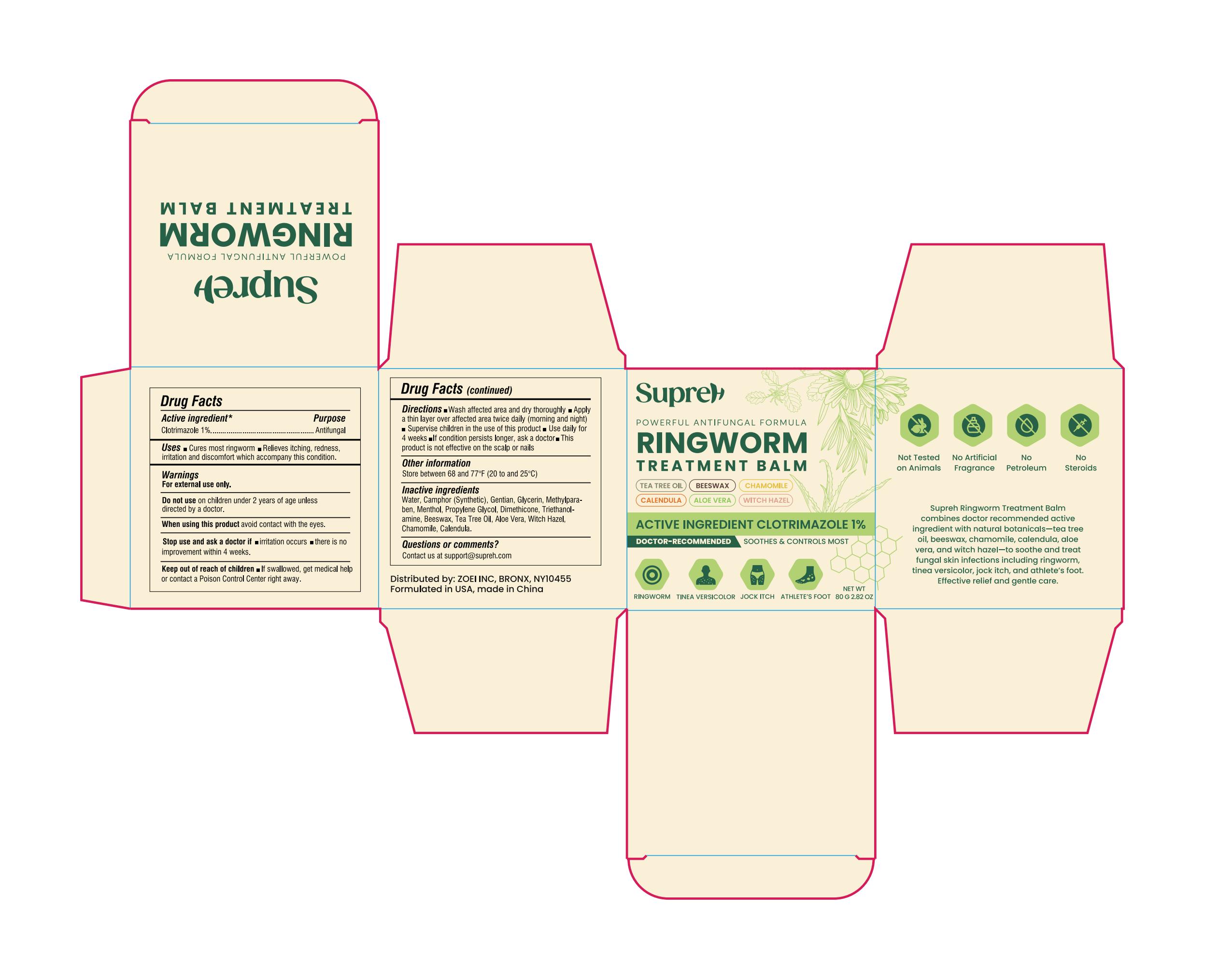 DRUG LABEL: SupreH Ringworm Treatment Balm
NDC: 83818-022 | Form: CREAM
Manufacturer: Shenzhen Xinxin Yunhai Technology Co., Ltd.
Category: otc | Type: HUMAN OTC DRUG LABEL
Date: 20250816

ACTIVE INGREDIENTS: CLOTRIMAZOLE 1 g/100 g
INACTIVE INGREDIENTS: WITCH HAZEL; PROPYLENE GLYCOL; DIMETHICONE; TRIETHANOLAMINE; CAMPHOR (SYNTHETIC); ARCTOTHECA CALENDULA WHOLE; MELALEUCA ALTERNIFOLIA (TEA TREE) LEAF OIL; WHITE WAX; GENTIAN VIOLET; METHYLPARABEN; MENTHOL; ALOE VERA LEAF; BIS(2-CHLOROETHYL)ETHER

83818-022

Active Ingredient

Clotrimazole 1%

Purpose

Antifungal

Use

cures most ringworm; relieves itching, redness, irritation and discomfort which accompany this condition

Warnings

For external use only. Do not use on children under 2 years of age unless directed by a doctor.

Do not use

on children under 2 years of age unless directed by a doctor.

When Using this product

avoid contact with the eyes

Stop use and ask a doctor if

irritation occurs; there is no improvement within 4 weeks

Stop use and ask a doctor if

irritation occurs; there is no improvement within 4 weeks

Keep Out Of Reach Of Children

If swallowed, get medical help or contact a Poison Control Center right away.

Directions

wash affected area and dry thoroughly; apply a thin layer over affected area twice daily (morning and night); supervise children in the use of this product; use daily for 4 weeks; if condition persists longer, ask a doctor; this product is not effective on the scalp or nails

Other information

Store between 68 to 77 F (20 to 25 C)

Inactive ingredients

Water, Camphor (Synthetic), Gentian, Glycerin, Methylparaben, Menthol, Propylene Glycol, Dimethicone, Triethanolamine, Beeswax, Tea Tree Oil, Aloe Vera, Witch Hazel, Chamomile, Calendula

Questions or comments?

Contact us at support@soothpro.com